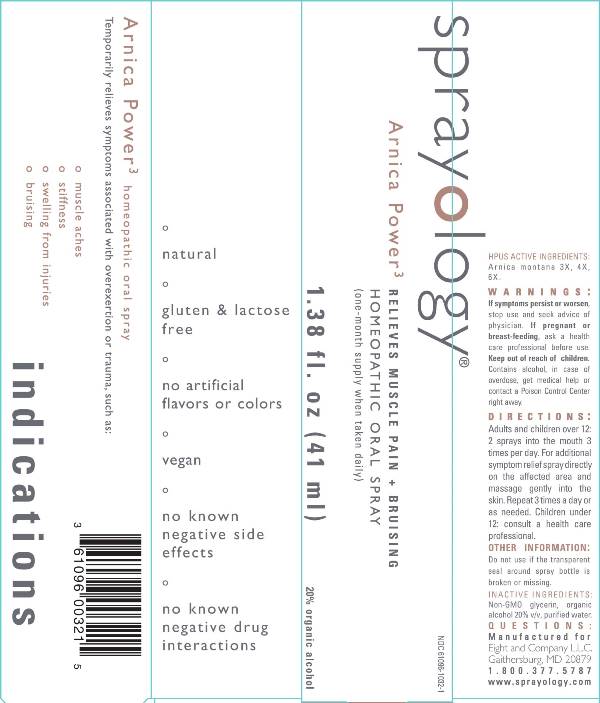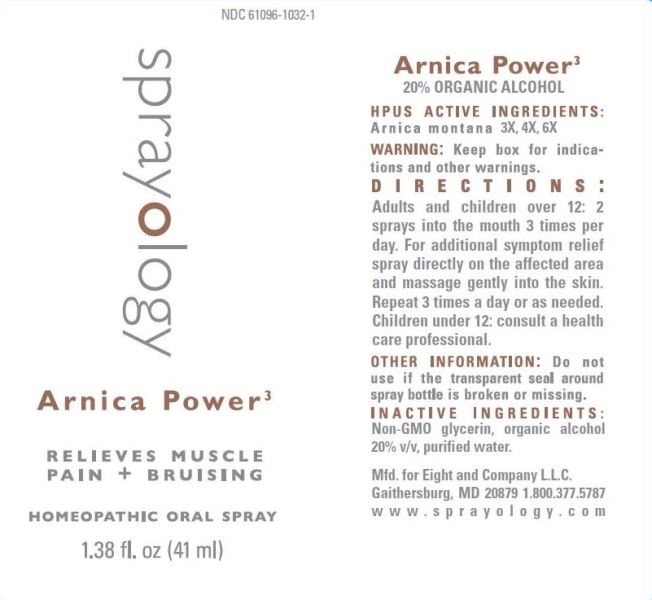 DRUG LABEL: Arnica Power
NDC: 61096-1032 | Form: LIQUID
Manufacturer: Eight and Company L.L.C
Category: homeopathic | Type: HUMAN OTC DRUG LABEL
Date: 20251218

ACTIVE INGREDIENTS: ARNICA MONTANA WHOLE 3 [hp_X]/41 mL
INACTIVE INGREDIENTS: GLYCERIN; ALCOHOL; WATER

Arnica Power

ACTIVE INGREDIENTS:

Arnica Montana 3X, 4X, 6X.

PURPOSE:

Temporarily relieves symptoms associated with overexertion or trauma, such as:

• muscle aches
• stiffness
• swelling from injuries
• bruising

WARNINGS:

If symptoms persist or worsen, stop use and seek advice of physician. If pregnant or breast-feeding, ask a health care professional before use. Keep out of reach of children. Contains alcohol, in case of overdose, get medical help or contact a Poison Control Center right away.

Keep out of reach of children. Contains alcohol, in case of overdose, get medical help or contact a Poison Control Center right away.

DIRECTIONS:

Adults and children over 12: 2 sprays into the mouth 3 times per day. For additional symptom relief spray directly on the affected area and massage gently into the skin. Repeat 3 times a day or as needed.

Children Under 12: consult a healthcare professional.

OTHER INFORMATION:

Do not use if the transparent seal around spray bottle is broken or missing.

INDICATIONS:

Temporarily relieves symptoms associated with overexertion or trauma, such as:

- muscle aches
- stiffness
- swelling from injuries
- bruising

° natural

° gluten & lactose free

° no artificial flavors or colors

° vegan

° no known negative side effects

° no known negative drug interactions

INACTIVE INGREDIENTS:

Non-GMO G=glycerin, organic alcohol 20% v/v, purified water.

QUESTIONS:

Mfd. for Eight and Company L.L.C.

Gaithersburg, MD 20878 1.800.377.5787

www.sprayology.com

PACKAGE LABEL DISPLAY:

Sprayology

Arnica Power3

RELIEVES MUSCLE PAIN + BRUISING

HOMEOPATHIC ORAL SPRAY

1.38 fl. oz (41 ml)